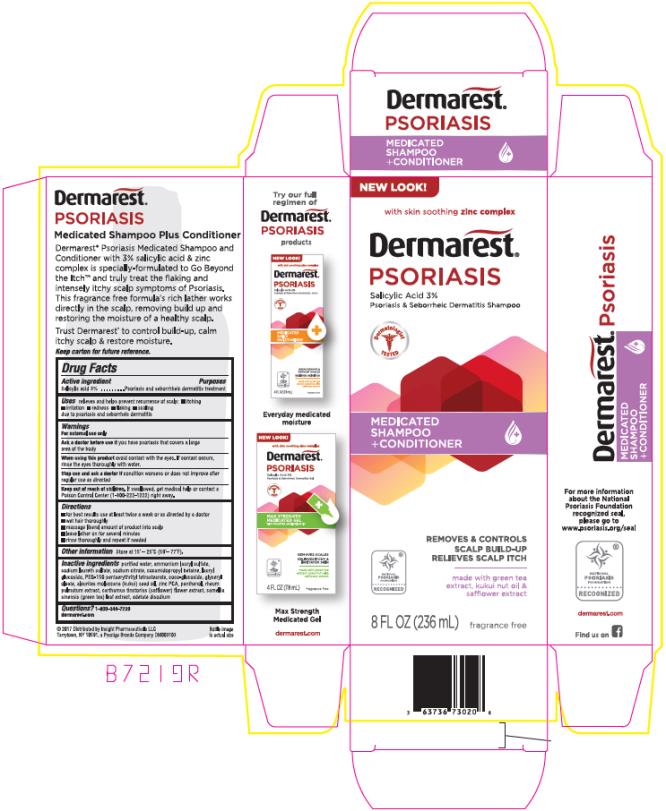 DRUG LABEL: Dermarest
NDC: 63736-302 | Form: LIQUID
Manufacturer: Insight Pharmaceuticals LLC
Category: otc | Type: HUMAN OTC DRUG LABEL
Date: 20241025

ACTIVE INGREDIENTS: SALICYLIC ACID 3 g/100 mL
INACTIVE INGREDIENTS: WATER; AMMONIUM LAURYL SULFATE; SODIUM LAURETH SULFATE; SODIUM CITRATE; COCAMIDOPROPYL BETAINE; LAURYL GLUCOSIDE; PEG-150 PENTAERYTHRITYL TETRASTEARATE; COCO GLUCOSIDE; GLYCERYL OLEATE; KUKUI NUT OIL; ZINC PIDOLATE; PANTHENOL; RHEUM PALMATUM WHOLE; SAFFLOWER; GREEN TEA LEAF; EDETATE DISODIUM

Dermarest Psoriasis Shampoo and Conditioner

Drug Facts

Active ingredient

Salicylic acid 3%

Purposes

Psoriasis and seborrhheic dermatitis treatment

Uses

relieves and helps prevent recurrence of scalp:

- itching
- irritation
- redness
- flaking
- scaling

due to psoriasis and seborrheic dermatitis

Warnings

For external use only

Ask a doctor before use if

you have psoriasis that covers a large area of the body

When using this product

avoid contact with the eyes. If contact occurs, rinse the eyes thoroughly with water.

Stop use and ask a doctor if

condition worsens or does not improve after regular use as directed

Keep out of reach of children.

If swallowed, get medical help or contact a Poison Control Center (1-800-222-1222) right away.

Directions

- for best results use at least twice a week or as directed by a doctor
- wet hair thoroughly
- massage liberal amount of product into scalp
- leave lather on for several minutes
- rinse thoroughly and repeat if needed

Other information

Store at 15° - 25°C (59° – 77°F)

Inactive ingredients

Purified water, ammonium lauryl sulfate, sodium laureth sulfate, sodium citrate, cocamidopropyl betaine, lauryl glucoside, PEG-150 pentaerythrityl tetrastearate, coco-glucoside, glyceryl oleate, aleurites moluccana seed oil, zinc PCA, panthenol, rheum palmatum extract, carthamus tinctorius (safflower) flower extract, camellia sinensis leaf extract, edetate disodium

Questions?

call 1-800-344-7239 dermarest.com

PRINCIPAL DISPLAY PANEL

- 236 ml Bottle Carton
Dermares®
Psoriasis
Salicylic Acid 3%
Psoriasis & Seborrheic Dermatitis Shampoo
Medicated Shampoo + Conditioner
8 FL OZ (236 mL)